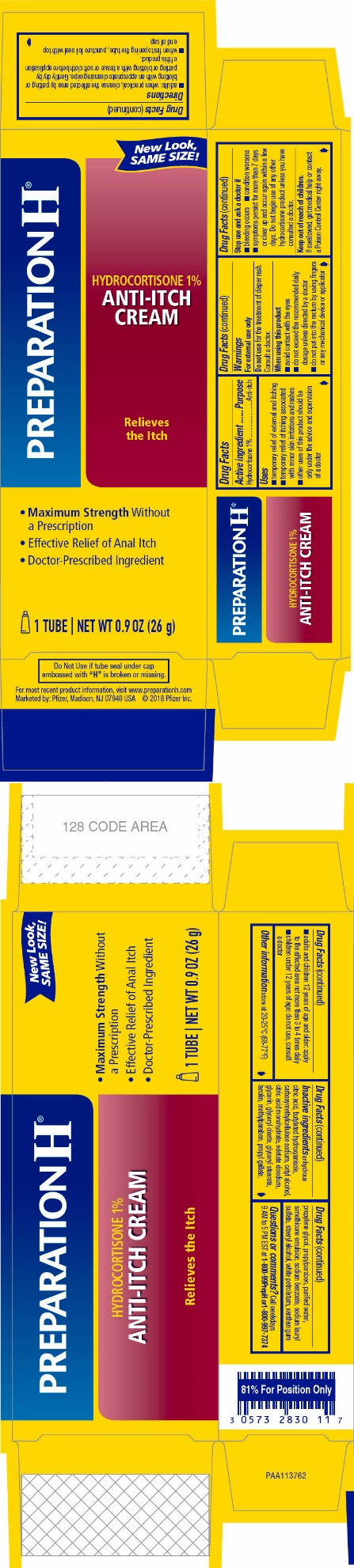 DRUG LABEL: PREPARATION H HYDROCORTISONE
NDC: 0573-2830 | Form: CREAM
Manufacturer: Haleon US Holdings LLC
Category: otc | Type: HUMAN OTC DRUG LABEL
Date: 20240229

ACTIVE INGREDIENTS: HYDROCORTISONE 10 mg/1 g
INACTIVE INGREDIENTS: ANHYDROUS CITRIC ACID; BUTYLATED HYDROXYANISOLE; CARBOXYMETHYLCELLULOSE SODIUM, UNSPECIFIED; CETYL ALCOHOL; CITRIC ACID MONOHYDRATE; EDETATE DISODIUM; GLYCERIN; GLYCERYL OLEATE; GLYCERYL MONOSTEARATE; LANOLIN; METHYLPARABEN; PROPYL GALLATE; PROPYLENE GLYCOL; PROPYLPARABEN; WATER; DIMETHICONE 350; SODIUM BENZOATE; SODIUM LAURYL SULFATE; STEARYL ALCOHOL; PETROLATUM; XANTHAN GUM

Drug Facts

ACTIVE INGREDIENT

Hydrocortisone 1%

PURPOSE

Anti-itch

USES

- temporary relief of external anal itching
- temporary relief of itching associated with minor skin irritations and rashes
- other uses of this product should be only under the advice and supervision of a doctor

WARNINGS

For external use only

Do not use

for the treatment of diaper rash. Consult a doctor.

When using this product

- avoid contact with the eyes
- do not exceed the recommended daily dosage unless directed by a doctor
- do not put into the rectum by using fingers or any mechanical device or applicator

Stop use and ask a doctor if

- bleeding occurs
- condition worsens
- symptoms persist for more than 7 days or clear up and occur again within a few days. Do not begin use of any other hydrocortisone product unless you have consulted a doctor.

Keep out of reach of children.

If swallowed, get medical help or contact a Poison Control Center right away.

DIRECTIONS

- adults: when practical, cleanse the affected area by patting or blotting with an appropriate cleansing wipe. Gently dry by patting or blotting with a tissue or soft cloth before application of this product.
- when first opening the tube, puncture foil seal with top end of cap
- adults and children 12 years of age and older: apply to the affected area not more than 3 to 4 times daily
- children under 12 years of age: do not use, consult a doctor

OTHER INFORMATION

store at 20-25°C (68-77°F)

INACTIVE INGREDIENTS

anhydrous citric acid, butylated hydroxyanisole, carboxymethylcellulose sodium, cetyl alcohol, citric acid monohydrate, edetate disodium, glycerin, glyceryl oleate, glyceryl stearate, lanolin, methylparaben, propyl gallate, propylene glycol, propylparaben, purified water, simethicone emulsion, sodium benzoate, sodium lauryl sulfate, stearyl alcohol, white petrolatum, xanthan gum

QUESTIONS OR COMMENTS?

Call weekdays 9 AM to 5 PM EST at 1-800-99PrepHor 1-800-997-7374.

PRINCIPAL DISPLAY PANEL

NDC 0573-2830-11

New Look,
SAME SIZE!

PREPARATION H®

HYDROCORTISONE 1%
ANTI-ITCH
CREAM

Relieves
the Itch

- Maximum StrengthWithout
  a Prescription
- Effective Relief of Anal Itch
- Doctor-Prescribed Ingredient

1 TUBE | NET WT 0.9 OZ (26 g)